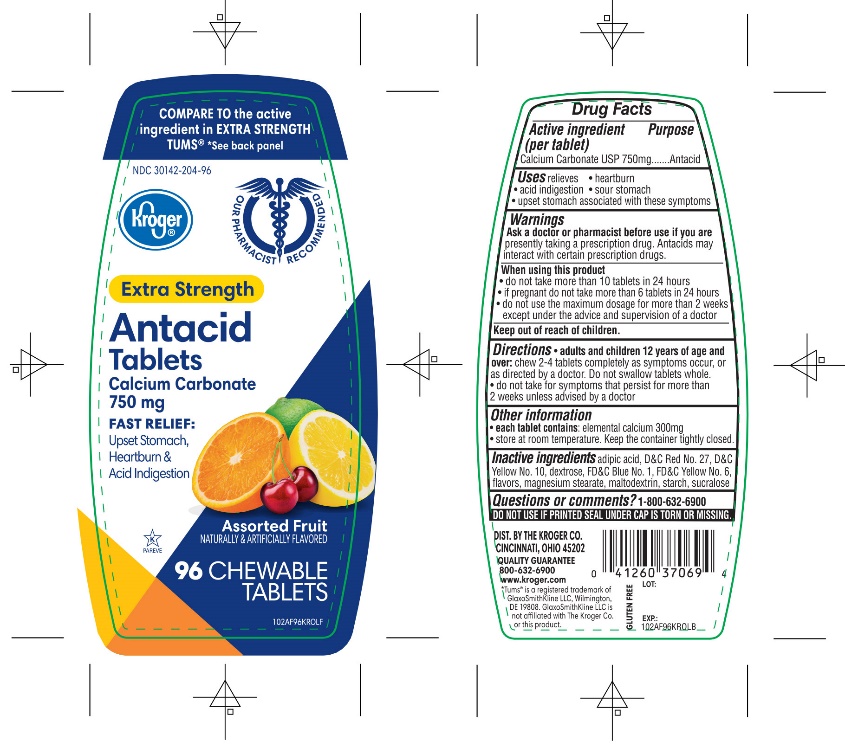 DRUG LABEL: Kroger Extra Strength

NDC: 30142-204 | Form: TABLET, CHEWABLE
Manufacturer: KROGER COMPANY
Category: otc | Type: HUMAN OTC DRUG LABEL
Date: 20250801

ACTIVE INGREDIENTS: CALCIUM CARBONATE 750 mg/1 1
INACTIVE INGREDIENTS: ADIPIC ACID; D&C RED NO. 27; D&C YELLOW NO. 10; DEXTROSE, UNSPECIFIED FORM; FD&C BLUE NO. 1; FD&C YELLOW NO. 6; MAGNESIUM STEARATE; MALTODEXTRIN; STARCH, CORN; SUCRALOSE; SUCROSE

Kroger®Extra Strength Assorted Fruits 96 Chewable Tablets

Active ingredient (per tablet)

Calcium Carbonate USP 750mg

Purpose

Antacid

Uses

relieves

- heartburn
- sour stomach
- acid indigestion
- upset stomach associated with these symptoms

Warnings

Ask a doctor or pharmacist before use if you arepresently taking a prescription drug. Antacids may interact with certain prescription drugs.

When using this product

- do not take more than 10 tablets in 24 hours
- if pregnant do not take more than 6 tablets in 24 hours
- do not use the maximum dosage for more than 2 weeks except under the advice and supervision of a doctor.

Directions

- chew 2-4 tablets completely as symptoms occur, or as directed by a doctor. Do not swallow tablets whole.
- do not take for symptoms that persist for more than 2 weeks unless advised by a doctor

Other information

- each tablet contains: elemental calcium 300 mg
- Store at room temperature. Keep the container tightly closed

Inactive ingredients

adipic acid, D&C Red No. 27, D&C Yellow No. 10, dextrose, FD &C Blue No. 1, FD&C Yellow No. 6, flavors, magnesium stearate, maltodextrin, starch, sucralose, sucrose

QUALITY GUARANTEE

1-800-632-6900

Package/Label Principal Display Panel

Kroger®

OUR PHARMACISTS RECOMMEND

NDC# 30142-204-96

COMPARE TO the active ingredients in EXTRA STRENGTH of TUMS®

EXTRA STRENGTH

Antacid Tablets

Calcium Carbonate 750 mg

Fast Relief of Upset Stomach, Heartburn, and Acid Indigestion

Assorted Fruit

Naturally and Artificially Flavored

96 CHEWABLE TABLETS

GLUTEN-FREE

QUALITY GUARANTEE

800-632-6900

DISTRIBUTED BY: THE KROGER CO. CINCINNATI, OHIO 45202

QUALITY GUARANTEE

800-632-6900

www.kroger.com

www.kroger.com

Tums®is a registered trademark of GlaxoSmithKline LLC, Wilmington, DE 19808. GlaxoSmithKline LLC is not affiliated with The Kroger Co. or this product.